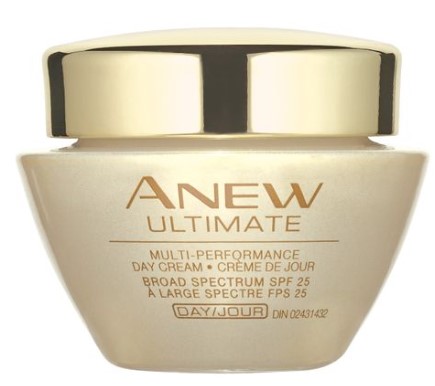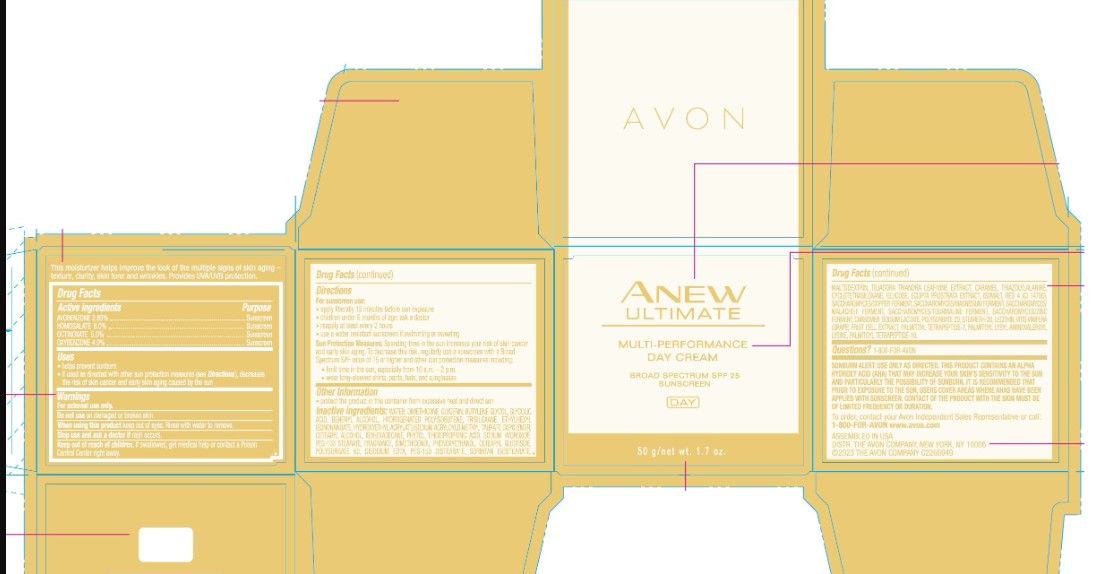 DRUG LABEL: ANEW ULTIMATE DAY MULTI-PERFORMANCECREAM SPF 25 SUNSCREEN
NDC: 68577-190 | Form: CREAM
Manufacturer: COSMAX USA, CORPORATION
Category: otc | Type: HUMAN OTC DRUG LABEL
Date: 20241220

ACTIVE INGREDIENTS: OCTINOXATE 5 mg/1 g; HOMOSALATE 8 mg/1 g; OXYBENZONE 4 mg/1 g; AVOBENZONE 2.85 mg/1 g
INACTIVE INGREDIENTS: GLYCOLIC ACID; LECITHIN, SOYBEAN; DIMETHICONE; CETEARYL ALCOHOL; PEG-100 STEARATE; PHENOXYETHANOL; PEG-150 DISTEARATE; HYDROGENATED POLYISOBUTENE (450 MW); TRISILOXANE; HYDROXYETHYL ACRYLATE/SODIUM ACRYLOYLDIMETHYL TAURATE COPOLYMER (45000 MPA.S AT 1%); THIODIPROPIONIC ACID; POLYSORBATE 60; MALTODEXTRIN; ISOHEXADECANE; CETEARYL GLUCOSIDE; EDETATE DISODIUM; CARAMEL; CYCLOTETRASILOXANE; WATER; GLYCERIN; BUTYLENE GLYCOL; POLYSORBATE 20; PALMITOYL TETRAPEPTIDE-10; BEHENYL ALCOHOL; ETHYLHEXYL ISONONANOATE; PHYTOL; SODIUM HYDROXIDE; DIMETHICONOL (2000 CST); SORBITAN ISOSTEARATE; THIAZOLYLALANINE; GLUCOSE; ECLIPTA PROSTRATA LEAF; ISOMALT; RED 4; SODIUM LACTATE; STEARETH-20; PALMITOYL TETRAPEPTIDE-7

AVON Anew Ultimate Multi-Performance Day Cream SPF 25

Active Ingredients

AVOBENZONE 2.85%
HOMOSALATE 8.0%
OCTINOXATE 5.0%
OXYBENZONE 4.0%

Purpose

Sunscreen

USES

- helps prevent sunburn
- if used as directed with other sun protection measures (see Directions), decrease the risk of skin cancer and early skin aging caused by the sun

Warnings

For external use only.

Do not use on damaged or broken skin.

When using this product keep out of eyes. Rinse with water to remove.

Stop use and ask a doctor if rash occurs.

Keep out of reach of children. If swallowed, get medical help or contact a Poison Control Center right away.

DIRECTIONS

For sunscreen use:

- apply liberally 15 minutes before sun exposure
- children less than 6 months of age: ask a doctor
- reapply at least every 2 hours
- use a water resistant sunscreen if swimming or sweating

Sun Protection Measures: Spending time in the sun increases your risk of skin cancer and early skin aging. To decrease this risk, regularly use a sunscreen with a Broad Spectrum SPF value of 15 or higher and other sun protection measures including:

- limit time in the sun, especially from 10 a.m. – 2 p.m.
- wear long-sleeved shirts, pants, hats, and sunglasses

OTHER INFORMATION

• protect the product in this container from excessive heat and direct sun

Inactive Ingredients:

WATER, DIMETHICONE, GLYCERIN, BUTYLENE GLYCOL, GLYCOLIC ACID, BEHENYL ALCOHOL, HYDROGENATED POLYISOBUTENE, TRISILOXANE, ETHYLHEXYL ISONONANOATE, HYDROXYETHYL ACRYLATE/SODIUM ACRYLOYLDIMETHYL TAURATE COPOLYMER, CETEARYL ALCOHOL, ISOHEXADECANE, PHYTOL, THIODIPROPIONIC ACID, SODIUM HYDROXIDE, PEG-100 STEARATE, FRAGRANCE, DIMETHICONOL, PHENOXYETHANOL, CETEARYL GLUCOSIDE, POLYSORBATE 60, DISODIUM EDTA, PEG-150 DISTEARATE, SORBITAN ISOSTEARATE, MALTODEXTRIN, TILIACORA TRIANDRA LEAF/VINE EXTRACT, CARAMEL, THIAZOLYLALANINE, CYCLOTETRASILOXANE, GLUCOSE, ECLIPTA PROSTRATA EXTRACT, ISOMALT, RED 4 (CI 14700), SACCHAROMYCES/COPPER FERMENT, SACCHAROMYCES/MAGNESIUM FERMENT, SACCHAROMYCES/MALACHITE FERMENT, SACCHAROMYCES/TOURMALINE FERMENT, SACCHAROMYCES/ZINC FERMENT, CARBOMER, SODIUM LACTATE, POLYSORBATE 20, STEARETH-20, LECITHIN, VITIS VINIFERA (GRAPE) FRUIT CELL EXTRACT, PALMITOYL TETRAPEPTIDE-7, PALMITOYL LYSYL AMINOVALEROYL LYSINE, PALMITOYL TETRAPEPTIDE-10